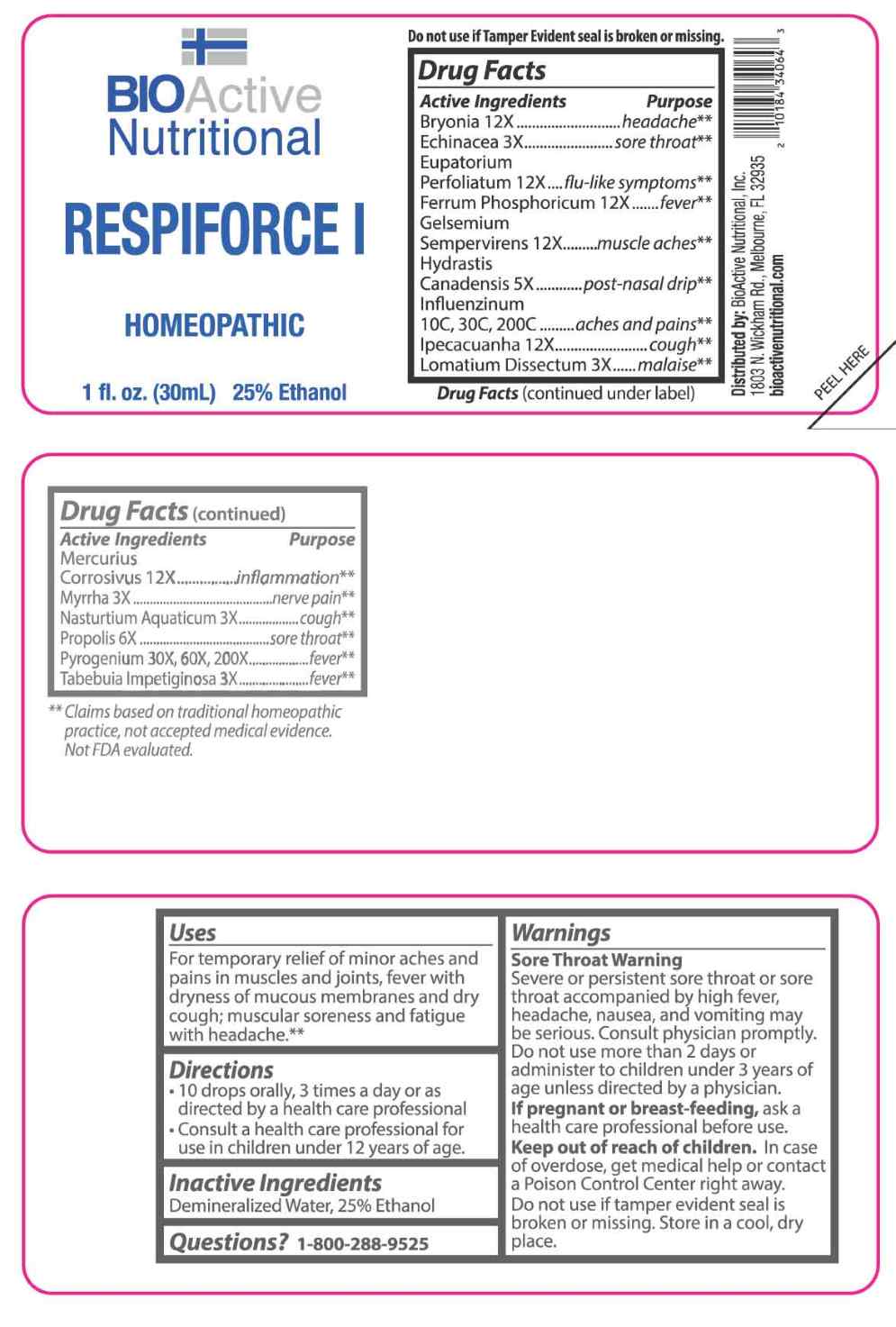 DRUG LABEL: Respiforce I
NDC: 43857-0661 | Form: LIQUID
Manufacturer: BioActive Nutritional, Inc.
Category: homeopathic | Type: HUMAN OTC DRUG LABEL
Date: 20251230

ACTIVE INGREDIENTS: ECHINACEA ANGUSTIFOLIA WHOLE 3 [hp_X]/1 mL; LOMATIUM DISSECTUM ROOT 3 [hp_X]/1 mL; MYRRH 3 [hp_X]/1 mL; NASTURTIUM OFFICINALE 3 [hp_X]/1 mL; HANDROANTHUS IMPETIGINOSUS BARK 3 [hp_X]/1 mL; GOLDENSEAL 5 [hp_X]/1 mL; PROPOLIS WAX 6 [hp_X]/1 mL; BRYONIA ALBA ROOT 12 [hp_X]/1 mL; EUPATORIUM PERFOLIATUM FLOWERING TOP 12 [hp_X]/1 mL; FERROSOFERRIC PHOSPHATE 12 [hp_X]/1 mL; GELSEMIUM SEMPERVIRENS ROOT 12 [hp_X]/1 mL; IPECAC 12 [hp_X]/1 mL; MERCURIC CHLORIDE 12 [hp_X]/1 mL; RANCID BEEF 30 [hp_X]/1 mL; INFLUENZA A VIRUS A/VICTORIA/4897/2022 IVR-238 (H1N1) ANTIGEN (FORMALDEHYDE INACTIVATED) 10 [hp_C]/1 mL; INFLUENZA A VIRUS A/THAILAND/8/2022 IVR-237 (H3N2) ANTIGEN (FORMALDEHYDE INACTIVATED) 10 [hp_C]/1 mL; INFLUENZA B VIRUS B/AUSTRIA/1359417/2021 BVR-26 WHOLE 10 [hp_C]/1 mL; INFLUENZA B VIRUS B/PHUKET/3073/2013 BVR-1B WHOLE 10 [hp_C]/1 mL
INACTIVE INGREDIENTS: WATER; ALCOHOL

DRUG FACTS:

ACTIVE INGREDIENTS:

Bryonia 12X, Echinacea 3X, Eupatorium Perfoliatum 12X, Ferrum Phosphoricum 12X, Gelsemium Sempervirens 12X, Hydrastis Canadensis 5X, Influenzinum 10C, 30C, 200C, Ipecacuanha 12X, Lomatium Dissectum 3X, Mercurius Corrosivus 12X, Myrrha 3X, Nasturtium Aquaticum 3X, Propolis 6X, Pyrogenium 30X, 60X, 200X, Tabebuia Impetiginosa 3X.

PURPOSE:

Bryonia - headache,** Echinacea – sore throat,** Eupatorium Perfoliatum – flu-like symptoms,** Ferrum Phosphoricum - fever,** Gelsemium Sempervirens – muscle aches,** Hydrastis Canadensis – post-nasal drip,** Influenzinum – aches and pains,** Ipecacuanha - cough,** Lomatium Dissectum - malaise,** Mercurius Corrosivus - inflammation,** Myrrha – nerve pain,** Nasturtium Aquaticum - cough,** Propolis – sore throat,** Pyrogenium - fever,** Tabebuia Impetiginosa – fever**

**Claims based on traditional homeopathic practice, not accepted medical evidence. Not FDA evaluated.

USES:

For temporary relief of minor aches and pains in muscles and joints, fever with dryness of mucous membranes and dry cough; muscular soreness and fatigue with headache.**

**Claims based on traditional homeopathic practice, not accepted medical evidence. Not FDA evaluated.

WARNINGS:

Sore Throat Warning

Severe or persistent sore throat or sore throat accompanied by high fever, headache, nausea, and vomiting may be serious. Consult physician promptly. Do not use more than 2 days or administer to children under 3 years of age unless directed by a physician.

If pregnant or breast-feeding, ask a health care professional before use.

Keep out of reach of children. In case of overdose, get medical help or contact a Poison Control Center right away.

Do not use if tamper evident seal is broken or missing.

Store in a cool, dry place.

KEEP OUT OF REACH OF CHILDREN:

In case of overdose, get medical help or contact a Poison Control Center right away.

DIRECTIONS:

• 10 drops orally, 3 times a day or as directed by a health care professional.

• Consult a health care professional for use in children under 12 years of age.

INACTIVE INGREDIENTS:

Demineralized Water, 25% Ethanol

QUESTIONS:

Distributed by:
BioActive Nutritional, Inc.
1803 N. Wickham Rd.
Melbourne, FL 32935
bioactivenutritional.com

1-800-288-9525

PACKAGE LABEL DISPLAY:

BIOActive Nutritional

RESPIFORCE I

HOMEOPATHIC

1 fl. oz. (30 mL)